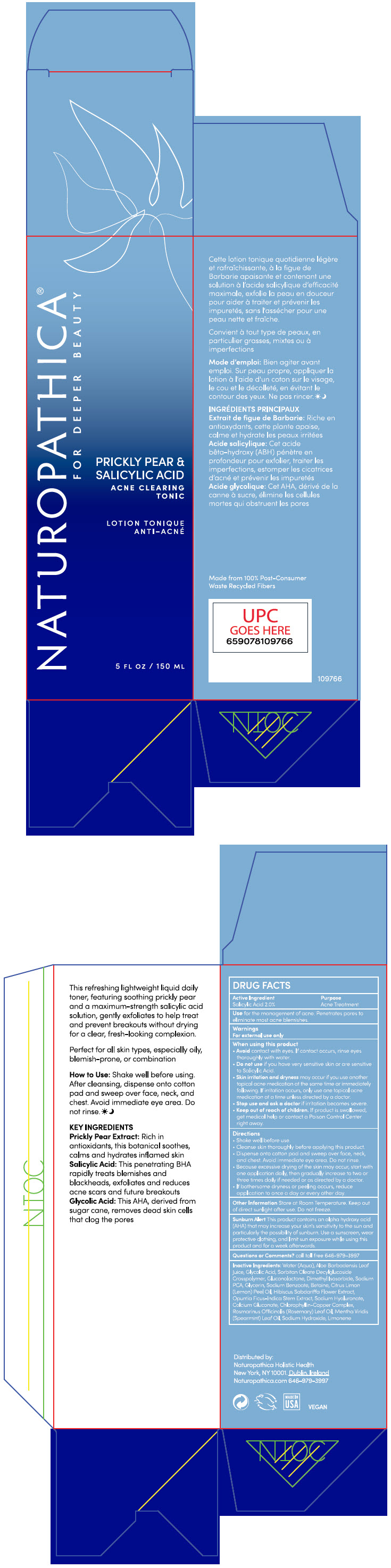 DRUG LABEL: PRICKLY PEAR and SALICYLIC ACID ACNE CLEARING TONIC
NDC: 64657-003 | Form: LIQUID
Manufacturer: Naturopathica Holistic Health
Category: otc | Type: HUMAN OTC DRUG LABEL
Date: 20240530

ACTIVE INGREDIENTS: SALICYLIC ACID 2 g/100 mL
INACTIVE INGREDIENTS: WATER; ALOE VERA LEAF; GLYCOLIC ACID; GLUCONOLACTONE; DIMETHYL ISOSORBIDE; SODIUM PYRROLIDONE CARBOXYLATE; GLYCERIN; SODIUM BENZOATE; BETAINE; LEMON OIL, COLD PRESSED; HIBISCUS SABDARIFFA FLOWER; OPUNTIA FICUS-INDICA STEM; HYALURONATE SODIUM; CALCIUM GLUCONATE; SODIUM COPPER CHLOROPHYLLIN; ROSEMARY OIL; SPEARMINT OIL; SODIUM HYDROXIDE; LIMONENE, (+)-

PRICKLY PEAR and SALICYLIC ACID ACNE CLEARING TONIC

Active Ingredients

Salicylic Acid 2.0%

Purpose

Acne Treatment

Use

- for the management of acne.
- Penetrates pores to eliminate most acne blemishes.

Warnings

For external use only

When using this product

- Avoid contact with eyes. If contact occurs, rinse eyes thoroughly with water.
- Do not use if you have very sensitive skin or are sensitive to Salicylic Acid.
- skin irritation and dryness may occur if you use another topical acne medication at the same time or immediately following. If irritation occurs, only use one topical acne medication at a time unless directed by a doctor.

Stop use and ask a doctor

- If irritation becomes severe.

Keep out of reach of children.

If swallowed, get medical help or contact a Poison Control Center right away.

Directions

- Shake well before use.
- Cleanse skin thoroughly before applying this product.
- Dispense onto cotton pad and sweep over face, neck and chest. Avoid immediate eye area. Do not rinse.
- because excessive drying of the skin may occur, start with one application daily, then gradually increase to two or three times daily if needed or as directed by a doctor.
- if bothersome dryness or peeling occurs, reduce application to once a day or every other day.

Other Information

Store at Room Temperature. Keep out of direct sunlight after use. Do not freeze.

Sunburn Alert

This product contains an alpha hydroxy acid (AHA) that may increase your skin's sensitivity to the sun and particularly the possibility of sunburn. Use a sunscreen, wear protective clothing, and limit sun exposure while using this product and for a week afterwards.

Inactive Ingredients

Water (Aqua), Aloe Barbadensis Leaf Juice ,Glycolic Acid, Sorbitan Oleate Decylglucoside Crosspolymer, Gluconolactone, Dimethyl Isosorbide, Sodium PCA, Glycerin, Sodium Benzoate, Betaine, Citrus Limon (Lemon) Peel Oil, Hibiscus Sabdariffa Flower Extract, Opuntia Ficus-Indica Stem Extract, Sodium Hyaluronate, Calcium Gluconate ,Chlorophyllin-Copper Complex, Rosmarinus Officinalis (Rosemary) Leaf Oil ,Mentha Viridis (Spearmint) Leaf Oil ,Sodium Hydroxide ,Limonene.

Questions or Comments?

call toll free 646-979-3997

Distributed by:
Naturopathica Holistic Health
New York, NY 10001.

PRINCIPAL DISPLAY PANEL - 150 ML Bottle Carton

NATUROPATHICA®
FOR DEEPER BEAUTY

PRICKLY PEAR &
SALICYLIC ACID
ACNE CLEARING
TONIC

5 FL OZ / 150 ML